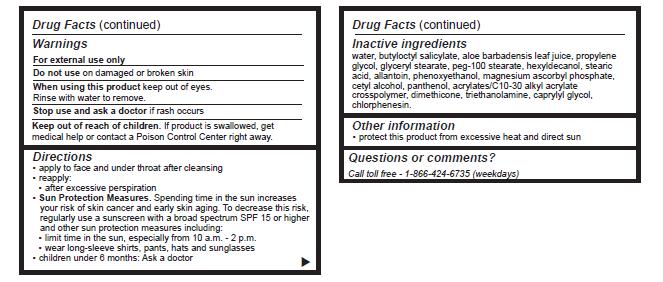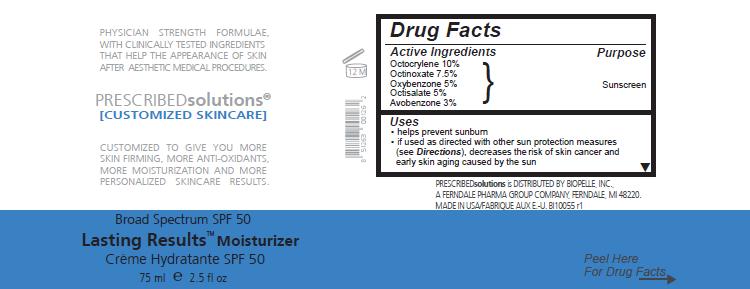 DRUG LABEL: Lasting Results Moisturizer
NDC: 42485-007 | Form: LOTION
Manufacturer: Biopelle, Inc.
Category: otc | Type: HUMAN OTC DRUG LABEL
Date: 20120501

ACTIVE INGREDIENTS: OCTOCRYLENE 100 mg/1 mL; OCTINOXATE 75 mg/1 mL; OXYBENZONE 50 mg/1 mL; OCTISALATE 50 mg/1 mL; AVOBENZONE 30 mg/1 mL
INACTIVE INGREDIENTS: WATER; BUTYLOCTYL SALICYLATE; ALOE VERA LEAF; PROPYLENE GLYCOL; GLYCERYL MONOSTEARATE; PEG-100 STEARATE; HEXYLDECANOL; STEARIC ACID; ALLANTOIN; PHENOXYETHANOL; MAGNESIUM ASCORBYL PHOSPHATE; CETYL ALCOHOL; PANTHENOL; CARBOMER INTERPOLYMER TYPE A (55000 MPA.S); DIMETHICONE; TROLAMINE; CAPRYLYL GLYCOL; CHLORPHENESIN

Lasting Results Moisturizer Broad Spectrum SPF 50

Active Ingredients

Octocrylene 10%

Octinoxate 7.5%

Oxybenzone 5%

Octisalate 5%

Avobenzone 3%

Purpose

Sunscreen

Uses

- helps prevent sunburn
- if used as directed with other sun protection measures (see Directions), decreases the risk of skin cancer and early skin aging caused by the sun

Warnings

For external use only

Do not use on damaged or broken skin

When using this product keep out of eyes.

Rinse with water to remove.

Stop use and ask a doctor if rash occurs

KEEP OUT OF REACH OF CHILDREN

Keep out of each of children. If product is swallowed, get medical help or contact a Poison Control Center right away.

Directions

- apply to face and under throat after cleansing
- reapply:
-
  - after excessive perspiration
- Sun Protection Measures. Spending time in the sun increases your risk of skin cancer and early skin aging. To decrease this risk, regularly use a sunscreen with a broad spectrum SPF 15 or higher and other sun protection measures including:
-
  - limit time in the sun, especially from 10 a.m. - 2 p.m.
-
  - wear long-sleeve shirts, pants, hats and sunglasses
- children under 6 months: Ask a doctor

Inactive ingredients

water, butyloctyl salicylate, aloe barbadensis leaf juice, propylene glycol, glyceryl stearate, peg-100 stearate, hexyldecanol, stearic acid, allantoin, phenoxyethanol, magnesium ascorbyl phosphate, cetyl alcohol, panthenol, acrylates/C10-30 alkyl acrylate crosspolymer, dimethicone, triethanolamine, caprylyl glycol, chlorphenesin.

Other information

- protect this product from excessive heat and direct sun

Questions or comments?

Call toll free - 1-866-424-6735 (weekdays)

Package Label

Principal Display

Peel Label